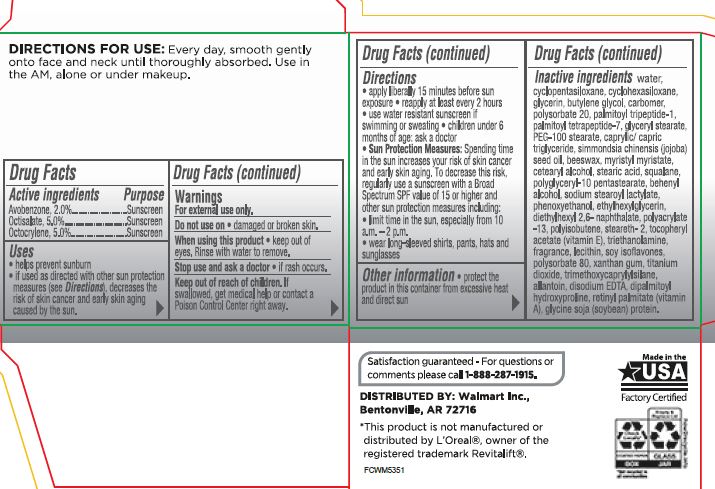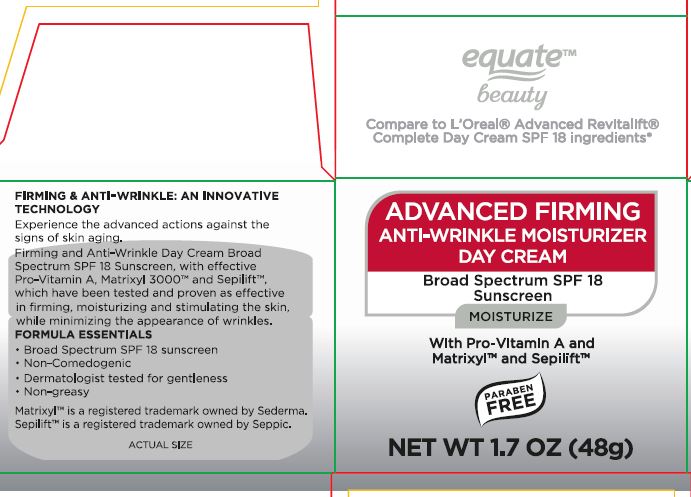 DRUG LABEL: Advanced Firming And Anti-Wrinkle Day SPF 18


NDC: 79903-206 | Form: CREAM
Manufacturer: Walmart
Category: otc | Type: HUMAN OTC DRUG LABEL
Date: 20240311

ACTIVE INGREDIENTS: AVOBENZONE 2 g/100 g; OCTISALATE 5 g/100 g
INACTIVE INGREDIENTS: OCTOCRYLENE 5 g/100 g; WATER; DIMETHICONE CROSSPOLYMER (450000 MPA.S AT 12% IN CYCLOPENTASILOXANE); CYCLOMETHICONE 6; GLYCERIN; BUTYLENE GLYCOL; CARBOMER 940; POLYSORBATE 20; PALMITOYL TRIPEPTIDE-1; PALMITOYL TETRAPEPTIDE-7; GLYCERYL STEARATE SE; PEG-100 STEARATE; MEDIUM-CHAIN TRIGLYCERIDES; JOJOBA OIL; YELLOW WAX; MYRISTYL MYRISTATE; CETOSTEARYL ALCOHOL; STEARIC ACID; SQUALANE; POLYGLYCERYL-10 PENTASTEARATE; SODIUM STEAROYL LACTYLATE; PHENOXYETHANOL; ETHYLHEXYLGLYCERIN; DIETHYLHEXYL 2,6-NAPHTHALATE; POLYACRYLATE-13; TROLAMINE; POLYISOBUTYLENE (2300 MW); STEARETH-2; .ALPHA.-TOCOPHEROL ACETATE; LECITHIN, SOYBEAN; SOY ISOFLAVONES; POLYSORBATE 80; XANTHAN GUM; TITANIUM DIOXIDE; TRIMETHOXYCAPRYLYLSILANE; ALLANTOIN; EDETATE DISODIUM ANHYDROUS; DIPALMITOYL HYDROXYPROLINE; VITAMIN A PALMITATE; SOY PROTEIN

PLSF-1850 Advanced Firming & Anti-Wrinkle Day Cream SPF 18

Active ingredients Purpose

Avonenzone 2% Sunscreen

Octisalate 5% Sunscreen

Octocrylene 5% Sunscreen

Uses

•helps prevent sunburn• If used as directed with other sun protection measures (see Oirections),decreases the risk of skin cancer and early skin aging caused by the sun.

Do not use on

• damaged or broken skin.

When using this product

•keep out of eyes. Rinse with waterto remove.

Stop use and ask a doctor

• if rash occurs.

Directions:

• apply liberal 15 minutes before sun exposure• reapply at least every 2 hours •use a water resistant sunscreen if swimmingor sweating•children under 6 months of age: ask a doctor• Sun Protection Measures:Spending time in the sun increase your risk of skin cancer and early skin aging. To decrease this risk. regularly usea sunscreen wrtha Broad Spectrum SPF value of15 or higher and other suncrin protection measures including:
• limrt time in the sun, especial from 10a.m. -2 p.rn.•wear long-sleeve shorts , pants, hats and sunglasses